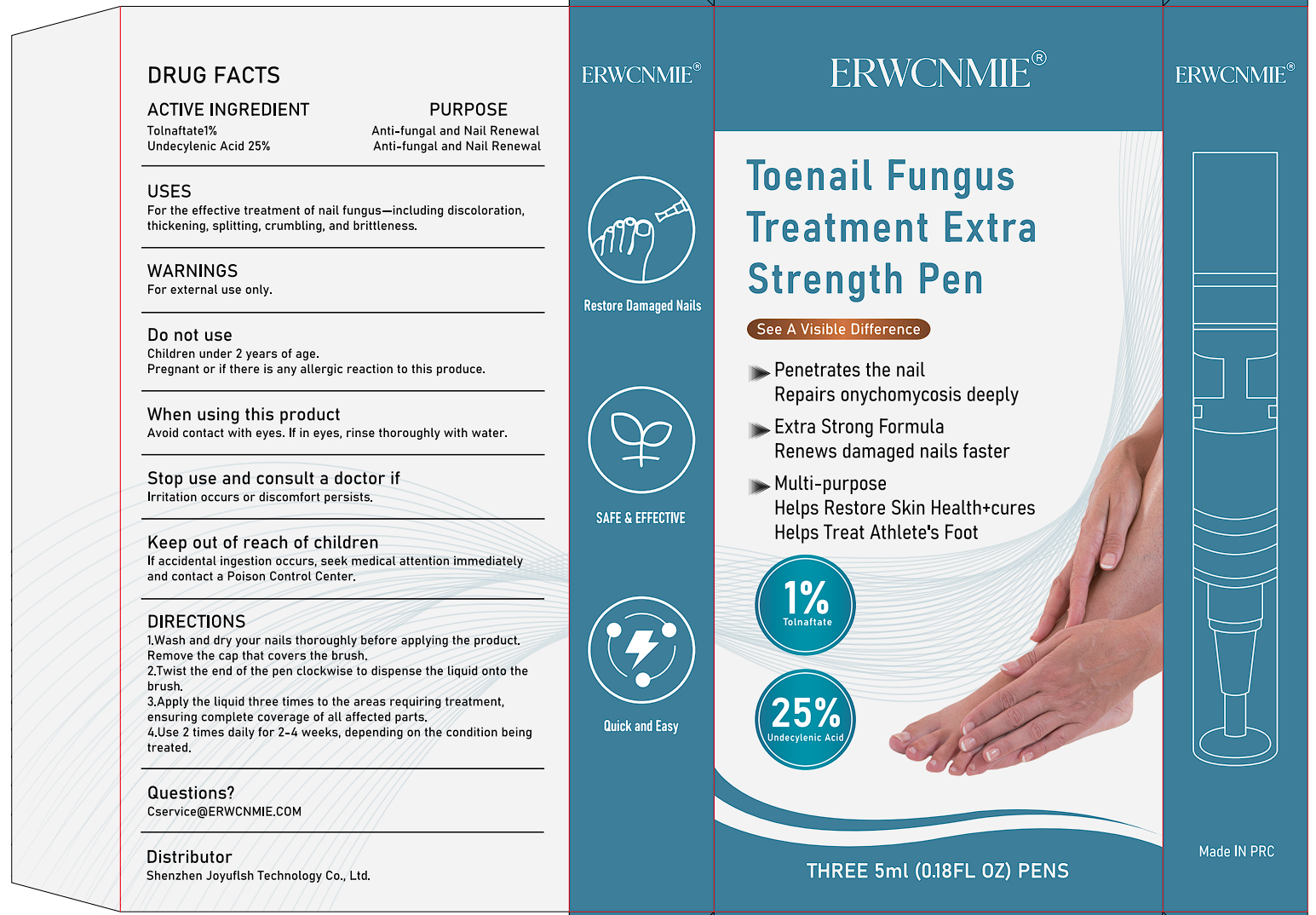 DRUG LABEL: ERWCNMIE Toenail Fungus Treatment Pen
NDC: 83766-108 | Form: LIQUID
Manufacturer: Shenzhen Joyuflsh Technology Co.,Ltd.
Category: otc | Type: HUMAN OTC DRUG LABEL
Date: 20250902

ACTIVE INGREDIENTS: TOLNAFTATE 1 g/100 mL; UNDECYLENIC ACID 25 g/100 mL
INACTIVE INGREDIENTS: ETHYLHEXYLGLYCERIN; PROPYLENE GLYCOL; LAUROCAPRAM; DIMETHICONE; GLYCERIN; C12-15 ALKYL LACTATE; PHENOXYETHANOL; SOPHORA FLAVESCENS ROOT; TOCOPHEROL; WATER; POLYETHYLENE GLYCOL, UNSPECIFIED; ALCOHOL

83766-108 ERWCNMIE Toenail Fungus Treatment Pen

ACTIVE INGREDIENT

Tolnaftate 1%
UNDECYLENIC ACID 25%

PURPOSE

Anti-fungal and Nail Renewal

INDICATIONS AND USAGE

For the effective treatment of nail fungus-including discoloration,.
thickening, splitting, crumbling, and brittleness.

WARNINGS

For external use only.

DO NOT USE

Children under 2 years of age.
Pregnant or if there is any allergic reaction to this produce.

WHEN USING

Avoid contact with eyes. lf in eyes, rinse thoroughly with water.

STOP USE

lrritation occurs or discomfort persists.

KEEP OUT OF REACH OF CHILDREN

If accidental ingestion occurs, seek medical attention immediatelyand contact a Poison Control Center.

DOSAGE AND ADMINISTRATION

1.Wash and dry your nails thoroughly before applying the product.Remove the cap that covers the brush.

2.Twist the end of the pen clockwise to dispense the liquid onto thebrush.
3.Apply the liquid three times to the areas requiring treatment,ensuring complete coverage of all affected parts.

4.Use 2 times daily for 2-4 weeks, depending on the condition beingtreated.

INACTIVE INGREDIENT

ALCOHOL
POLYETHYLENE GLYCOL
PROPYLENE GLYCOL
DIMETHICONE
C12-15 ALKYL LACTATE
ETHYLHEXYLGLYCERIN
GLYCERIN
LAUROCAPRAM
SOPHORA FLAVESCENS ROOT
TOCOPHEROL
PHENOXYETHANOL
WATER